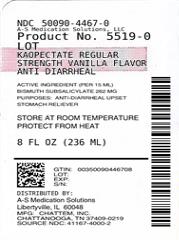 DRUG LABEL: Kaopectate Regular Strength Vanilla Flavor Anti Diarrheal
NDC: 50090-4467 | Form: LIQUID
Manufacturer: A-S Medication Solutions
Category: otc | Type: HUMAN OTC DRUG LABEL
Date: 20190828

ACTIVE INGREDIENTS: BISMUTH SUBSALICYLATE 262 mg/15 mL
INACTIVE INGREDIENTS: CARAMEL; CARBOXYMETHYLCELLULOSE SODIUM, UNSPECIFIED FORM; MICROCRYSTALLINE CELLULOSE; SODIUM SALICYLATE; SORBIC ACID; SUCROSE; WATER; XANTHAN GUM

Kaopectate Vanilla Flavor Anti-Diarrheal

Active Ingredient

(per 15mL):

Bismuth subsalicylate 262 mg

Purpose

Anti-diarrheal

Upset stomach reliever

Uses

- relieves diarrhea
- relieves nausea and upset stomach associated with this symptom

Warnings

Reye’s Syndrome:

Children and teenagers who have or are recovering from chicken pox or flu-like symptoms should not use this product. When using this product, if changes in behavior with nausea and vomiting occur, consult a doctor because these symptoms could be an early sign of Reye’s syndrome, a rare but serious illness.

Do not take if you are

- allergic to salicylates (including aspirin)
- taking other salicylate products

Do not use if you have

- an ulcer
- a bleeding problem
- bloody or black stool

Ask a doctor before use if you have

- fever
- mucus in the stool

Ask a doctor or pharmacist before use if you are taking any drug for

- diabetes
- gout
- arthritis
- anticoagulation (thinning the blood)

When using this product

a temporary, but harmless, darkening of the stool and/or tongue may occur

Stop use and ask a doctor if

- symptoms get worse
- ringing in the ears or loss of hearing occurs
- diarrhea lasts more than 2 days

If pregnant or breast-feeding,

ask a health professional before use.

Keep out of reach of children.

In case of overdose, get medical help or contact a Poison Control Center right away.

Directions

- shake well immediately before each use
- adults and children 12 years of age and older: 30 mL or 2 tablespoonfuls
- for accurate dosing, use convenient pre-measured dose cup
- repeat dose every 1/2 hour to 1 hour as needed
- do not exceed 8 doses in 24 hours
- use until diarrhea stops but not more than 2 days
- children under 12 years: ask a doctor
- drink plenty of clear fluids to help prevent dehydration caused by diarrhea

Other Information

- each 15 mL tablespoonful contains: sodium 4 mg
- each 15 mL tablespoonful contains: total salicylates 130 mg
- do not use if inner seal is broken or missing
- low sodium

Inactive Ingredients

caramel, carboxymethylcellulose sodium, flavor, microcrystalline cellulose, sodium salicylate, sorbic acid, sucrose, water, xanthan gum (245-241)

Dist. by CHATTEM, INC.

P.O. Box 2219

Chattanooga, TN 37409 USA

© 2008 Chattem, Inc.

Made in Canada

CHATTEM® www.chattem.com